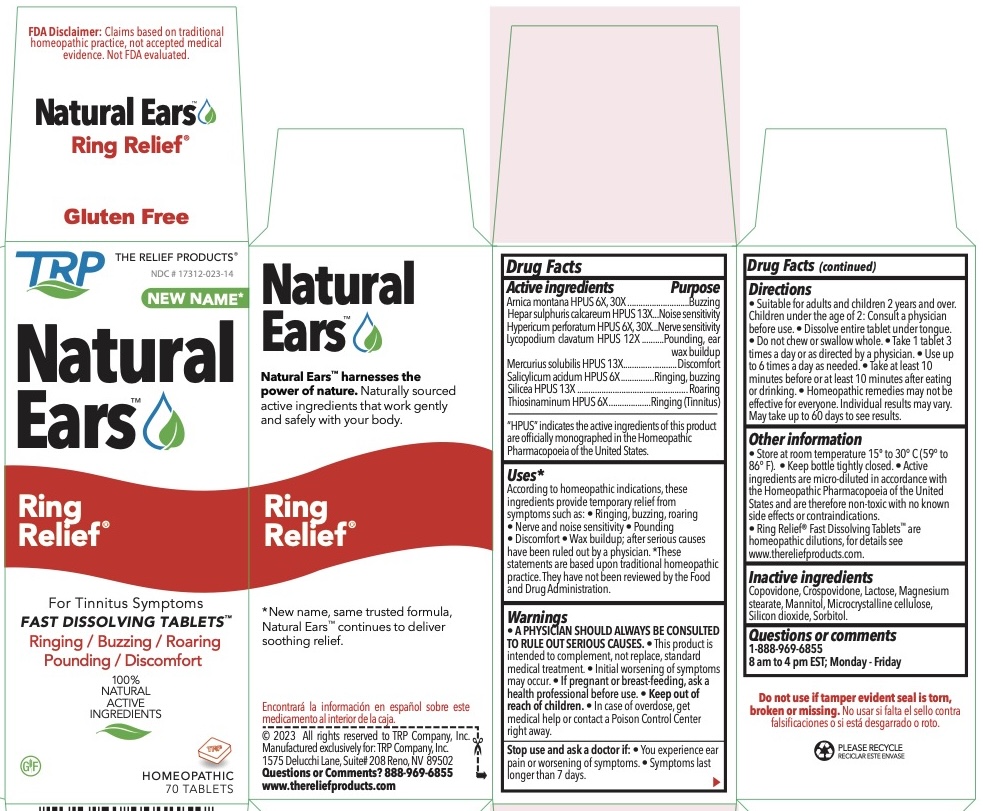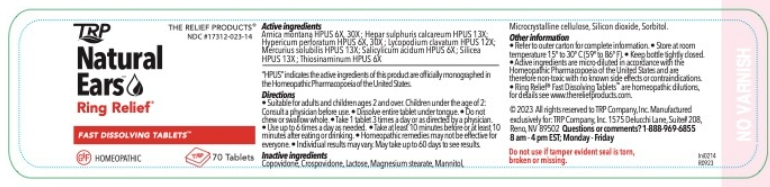 DRUG LABEL: Ring Relief
NDC: 17312-023 | Form: TABLET, ORALLY DISINTEGRATING
Manufacturer: TRP Company
Category: homeopathic | Type: HUMAN OTC DRUG LABEL
Date: 20251215

ACTIVE INGREDIENTS: ARNICA MONTANA 6 [hp_X]/1 1; CALCIUM SULFIDE 13 [hp_X]/1 1; HYPERICUM PERFORATUM 6 [hp_X]/1 1; LYCOPODIUM CLAVATUM SPORE 12 [hp_X]/1 1; MERCURIUS SOLUBILIS 13 [hp_X]/1 1; SALICYLIC ACID 6 [hp_X]/1 1; SILICON DIOXIDE 13 [hp_X]/1 1; ALLYLTHIOUREA 6 [hp_X]/1 1
INACTIVE INGREDIENTS: MANNITOL; SORBITOL; CROSPOVIDONE; CELLULOSE, MICROCRYSTALLINE; COPOVIDONE; LACTOSE; MAGNESIUM STEARATE

Ring Relief Homeopathic Fast Dissolving Tablets

ACTIVE INGREDIENT

Arnica montana HPUS 6x, 30x
Hepar sulph calc HPUS 13x
Hypericum perforatum HPUS 6x, 30x
Lycopodium clavatum HPUS 12x
Mercurius sol HPUS 13x
Salicylicum acidum HPUS 6x
Silicea HPUS 13x
Thiosinaminum HPUS 6x

PURPOSE

Arnica montana HPUS - Buzzing, Chirping
Hepar sulph calc HPUS - Noise sensitivity
Hypericum perforatum HPUS - Nerve sensitivity
Lycopodium clavatum HPUS - Pounding, wax buildup
Mercurius sol HPUS - Discomfort
Salicylicum acidum HPUS - Ringing, Buzzing
Silicea HPUS - Roaring
Thiosinaminum HPUS - Ringing (Tinnitus)

Uses*
According to homeopathic indications, these ingredients temporarily relieve Tinnitus symptoms such as: • Ringing • Buzzing • Roaring • Nerve and Noise Sensitivity • Pounding • Discomfort • Wax buildup after serious causes have been ruled out by a physician.
*These statements are based upon traditional homeopathic practice. They have not been reviewed by the Food and Drug Administration.

Warnings:
A PHYSICIAN SHOULD ALWAYS BE CONSULTED TO RULE OUT SERIOUS CAUSES.

- This product is intended to complement, not replace, standard medical treatment.
- Initial worsening of symptoms may occur.

PREGNANCY OR BREAST FEEDING

If pregnant or breast-feeding, ask a health professional before use.

Keep out of reach of children

WARNINGS

- In case of overdose, get medical help or contact a Poison Control Center right away.

Stop use and ask a doctor if:

- You experience ear pain or worsening symptoms.
- Symptoms last longer than 7 days.

Directions

- Suitable for adults and children ages 2 and over.
- Children under the age of 2: Consult a physician before use.
- Dissolve entire tablet under tongue.
- Do not chew or swallow whole.
- Take 1 tablet 3 times a day or as directed by a physician.
- Use up to 6 times a day as needed.
- Take at least 10 minutes before or at least 10 minutes after eating or drinking.
- Homeopathic remedies may not be effective for everyone.
- May take up to 60 days to see results.

Other information

- There are no known contraindications.
- Active ingredients are micro-diluted in accordance with the Homeopathic Pharmacopoeia of the United States and are therefore non-toxic with no known side effects.
- Store in a cool dark location.
- Ring Relief Fast Disolving Tablets are homeopathic dilutions: see www.thereliefproducts.com for details.

Inactive Ingredients
Advantol® 300, Lactose, Magnesium Stearate, Mannitol, Microcrystalline Cellulose.

Questions or comments? 888-969-6855
www.thereliefproducts.com